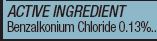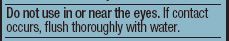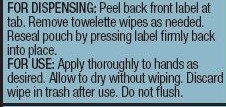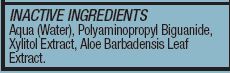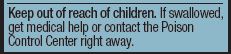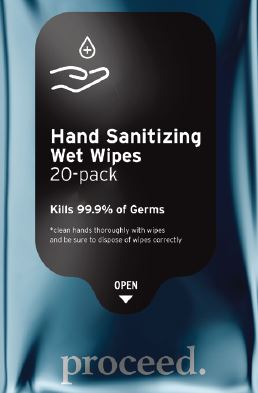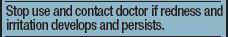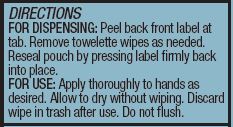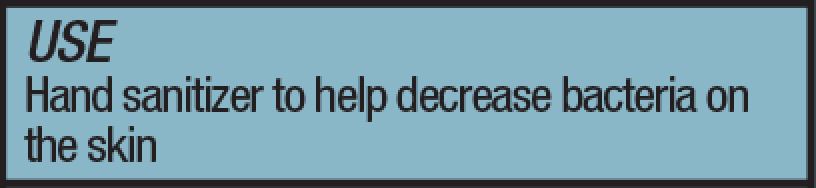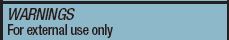 DRUG LABEL: Sanitizing Alcohol Free Wipes
NDC: 80380-100 | Form: CLOTH
Manufacturer: Shedrain Corporation
Category: otc | Type: HUMAN OTC DRUG LABEL
Date: 20201023

ACTIVE INGREDIENTS: BENZALKONIUM CHLORIDE 0.13 mg/100 mg
INACTIVE INGREDIENTS: POLYAMINOPROPYL BIGUANIDE 0.5 mg/100 mg; ALOE VERA LEAF 0.04 mg/100 mg; WATER 99.3 mg/100 mg; XYLITOL 0.03 mg/100 mg

Active Ingredient

Active ingredient for this sanitizing alcohol-free wipes is Benzalkonium chloride

.

Purpose

Hand Sanitizer to help decrease bacteria on the skin.

Use

For dispensing: Peel back front label at tab. Remove towelette wipes as needed. Reseal pouch by pressing label firmly back into place.

For use: Apply thoroughly to hands as desired. Allow to dry without wiping. Discard wipe in trash after use. Do not flush.

Warnings

For external use only.

Do not use in or near the eyes. If contact occurs, flush thoroughly with water.

Stop use and contact doctor if redness and irritation develops and persists.

Keep out of reach of children. If swallowed, get medical help or contact a Poison Control Center right away.

Inactive ingredients

Aqua (Water), Polyaminopropyl Biguanide, Xylitol Extract, Aloe Barbadensis Leaf Extract.

Dosage

FOR DISPENSING: Peel back front label at tab. Remove towelette wipes as needed.

FOR USE: Apply thoroughly to hands asdesired. Allow to dry without wiping.

Package Label - Principal Display Panel

20-pack. NDC: 80380-100-01

.